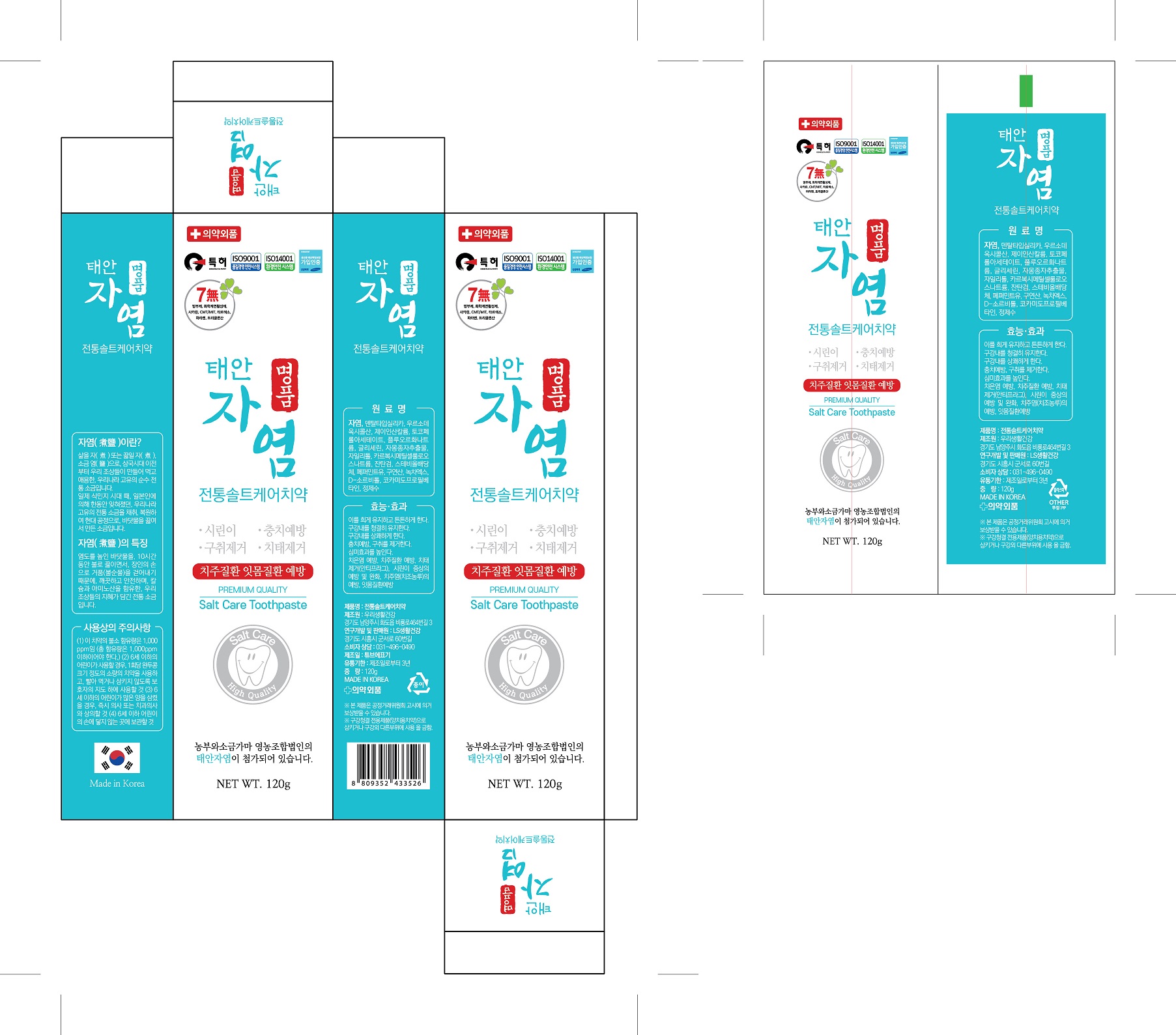 DRUG LABEL: Tradition Salt CareToothpaste
NDC: 73065-0007 | Form: PASTE, DENTIFRICE
Manufacturer: WOORILIFE&HEALTH
Category: otc | Type: HUMAN OTC DRUG LABEL
Date: 20210411

ACTIVE INGREDIENTS: SODIUM FLUORIDE 0.22 g/100 g
INACTIVE INGREDIENTS: XYLITOL; WATER

ACTIVE INGREDIENT

Sodium fluoride

PURPOSE

Tooth whitening, tooth deay prevention, bod breath removal. Makes teeth strong. Keeps the mouth c;ean. Refreshes the Inside of the mouth. Increases the aesthetic effect. Prevention of gum disease, removal of plaque (ant-plaque)

Keep out of reach of children

INDICATIONS AND USAGE

apply appropriate amount of the tooth paste on the tooth brush and brush the teeth

WARNINGS

Storage method

1. Keep it at room temperature in a classified container.

2. Cover and store at room temperature.

3. Store in a not moisture and cool place.

4. Air may come out during use of this product, but there is no problem with its weight.

Usage Precautions

1. Be careful not to swallow. Rinse mouth thoroughly after use

2. If the use of toothpaste causes abnormalities such as gums or mouth injury, discontinue use and consult a doctor or dentist.

3. For children under 6 years of age, use a small amount of toothpaste as small as pea per use, and use under the guidance of a guardian to avoid sucking or swallowing.

4. If a child under 6 years old swallows large amount, consult with a doctor or dentist immediately.

5. Keep out of the reach of children under 6 years of age.

INACTIVE INGREDIENT

Dental type Silica
Ursodeoxycholic Acid
Potassium Phosphate, Dibasic
Potassium Phosphate, Monobasic
Tocopherol Acetate
Glycerine
Grapefruit Seed Extract
Xylitol
Carboxymethylcellulose Sodium
Xanthan gum
Stevioside
Peppermint oil
sodium chloride
Citric acid
Green tea Extract
D-Sorbitol
dl-menthol
Cocamidopropyl Betaine
Purified Water

DOSAGE AND ADMINISTRATION

For dental use only